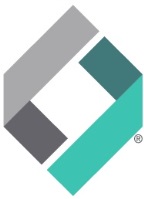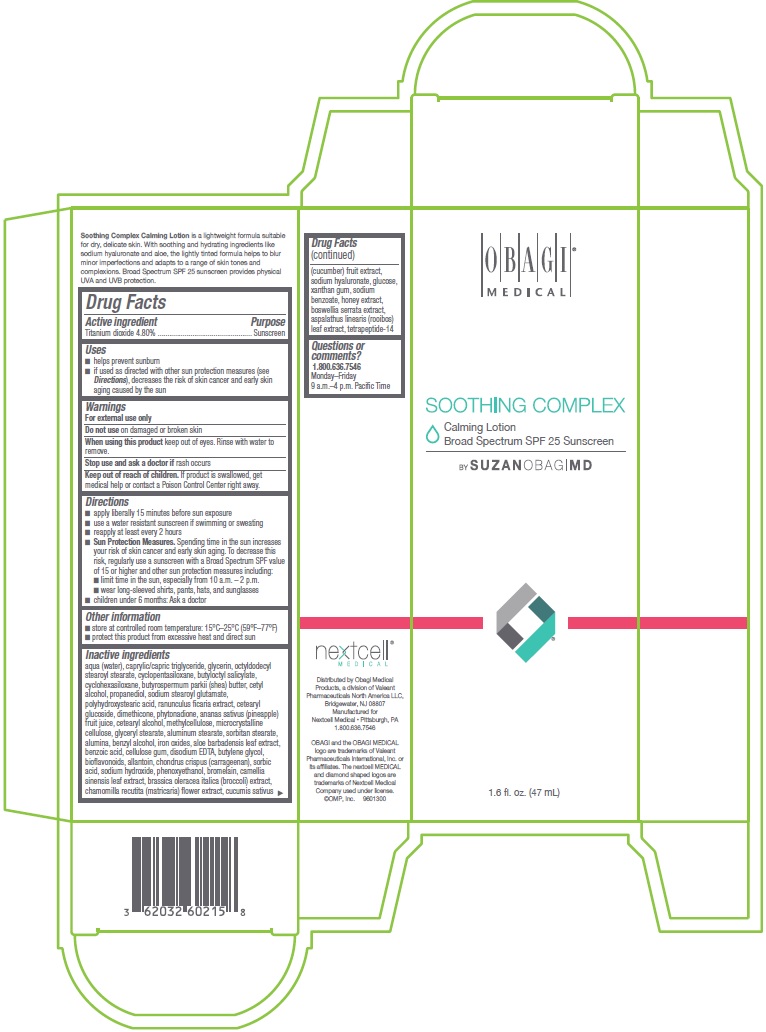 DRUG LABEL: NEXT CELL MEDICAL
NDC: 62032-602 | Form: LOTION
Manufacturer: OMP, Inc.
Category: otc | Type: HUMAN OTC DRUG LABEL
Date: 20180111

ACTIVE INGREDIENTS: TITANIUM DIOXIDE 480 mg/1 mL
INACTIVE INGREDIENTS: WATER; MEDIUM-CHAIN TRIGLYCERIDES; GLYCERIN; OCTYLDODECYL STEAROYL STEARATE; CYCLOMETHICONE 5; BUTYLOCTYL SALICYLATE; CYCLOMETHICONE 6; SHEA BUTTER; CETYL ALCOHOL; PROPANEDIOL; SODIUM STEAROYL GLUTAMATE; POLYHYDROXYSTEARIC ACID (2300 MW); RANUNCULUS FICARIA; CETEARYL GLUCOSIDE; DIMETHICONE; PHYTONADIONE; PINEAPPLE JUICE; CETOSTEARYL ALCOHOL; METHYLCELLULOSE (1500 MPA.S); MICROCRYSTALLINE CELLULOSE; GLYCERYL MONOSTEARATE; ALUMINUM MONOSTEARATE; SORBITAN MONOSTEARATE; ALUMINUM OXIDE; BENZYL ALCOHOL; FERROUS OXIDE; ALOE VERA LEAF; BENZOIC ACID; CARBOXYMETHYLCELLULOSE SODIUM, UNSPECIFIED FORM; EDETATE DISODIUM; BUTYLENE GLYCOL; CITRUS BIOFLAVONOIDS; ALLANTOIN; CHONDRUS CRISPUS CARRAGEENAN; SORBIC ACID; SODIUM HYDROXIDE; PHENOXYETHANOL; BROMELAINS; GREEN TEA LEAF; BROCCOLI SPROUT; CHAMOMILE; CUCUMBER; HYALURONATE SODIUM; DEXTROSE, UNSPECIFIED FORM; XANTHAN GUM; SODIUM BENZOATE; HONEY; INDIAN FRANKINCENSE; ASPALATHUS LINEARIS LEAF; TETRAPEPTIDE-4

OBAGI MEDICAL SOOTHING COMPLEX
Calming Lotion
Broad Spectrum SPF 25 Sunscreen

Active Ingredient

Titanium dioxide 4.80%

Purpose

Sunscreen

Uses

- helps prevent sunburn
- if used as directed with other sun protection measures (see Directions), decreases the risk of skin cancer and early skin aging caused by sun

Warnings

For external use only

Do Not Use

- on damaged or broken skin

When using this product

- keep out of eyes. Rinse with water to remove

Stop use and ask a doctor if

- rash occurs

Keep out of reach of children

- if product is swallowed, get medical help or contact a Poison Control Center right away.

Directions

- apply liberally 15 minutes before sun exposure
- use a water resistant sunscreen if swimming or sweating
- reapply at least every 2 hours
- Sun Protection Measures. Spending time in the sun increases your risk of skin cancer and early skin aging. To decrease this risk, regularly use a sunscreen with a Broad Spectrum SPF value of 15 or higher and other sun protection measures including:
  - limit time in the sun, especially from 10 a.m. – 2 p.m.
  - wear long-sleeved shirts, pants, hats, and sunglasses
- children under 6 months: Ask a doctor

Other information

- store at controlled room temperature: 15°C–25°C (59°F–77°F)
- protect this product from excessive heat and direct sun

Inactive Ingredients

aqua (water), caprylic/capric triglyceride, glycerin, octyldodecyl stearoyl stearate, cyclopentasiloxane, butyloctyl salicylate, cyclohexasiloxane, butyrospermum parkii (shea) butter, cetyl alcohol, propanediol, sodium stearoyl glutamate, polyhydroxystearic acid, ranunculus ficaria extract, cetearyl glucoside, dimethicone, phytonadione, ananas sativus (pineapple) fruit juice, cetearyl alcohol, methylcellulose, microcrystalline cellulose, glyceryl stearate, aluminum stearate, sorbitan stearate, alumina, benzyl alcohol, iron oxides, aloe barbadensis leaf extract, benzoic acid, cellulose gum, disodium EDTA, butylene glycol, bioflavonoids, allantoin, chondrus crispus (carrageenan), sorbic acid, sodium hydroxide, phenoxyethanol, bromelain, camellia sinensis leaf extract, brassica oleracea italica (broccoli) extract, chamomilla recutita (matricaria) flower extract, cucumis sativus (cucumber) fruit extract, sodium hyaluronate, glucose, xanthan gum, sodium benzoate, honey extract, boswellia serrata extract, aspalathus linearis (rooibos) leaf extract, tetrapeptide-14

Questions or comments?

1.800.636.7546

Monday–Friday 9 a.m.–4 p.m. Pacific Time

Principal Display Panel – 47 mL Label

OBAGI MEDICAL

SOOTHING COMPLEX

Calming Lotion

Broad Spectrum SPF 25 Sunscreen

BY SUZAN OBAGI MD

1.6 fl.oz. (47 mL)